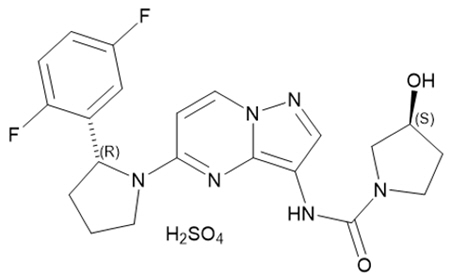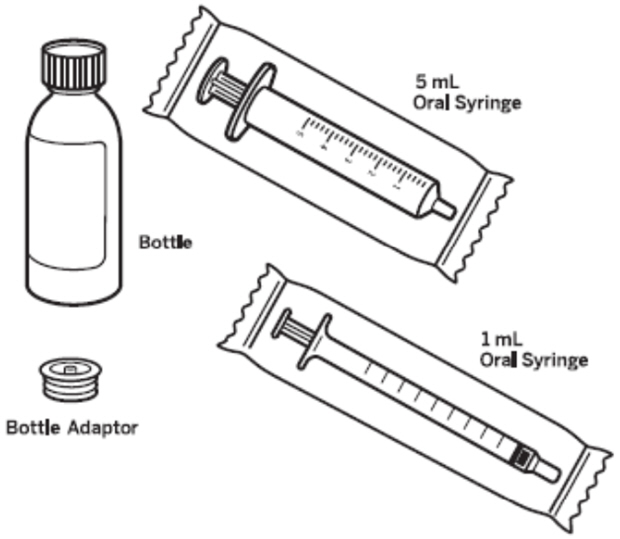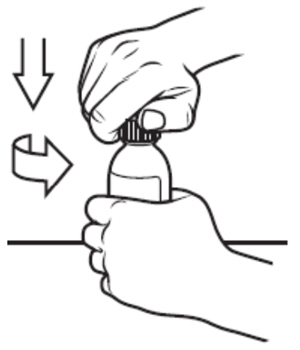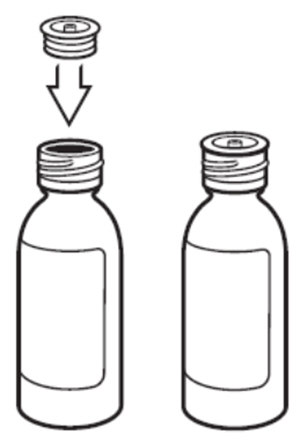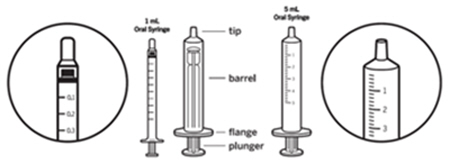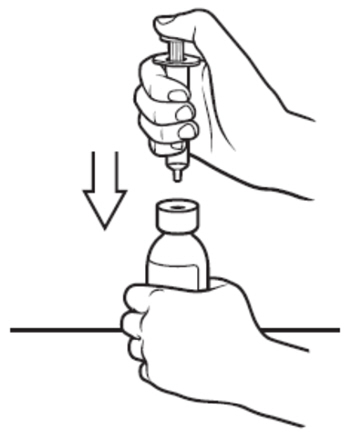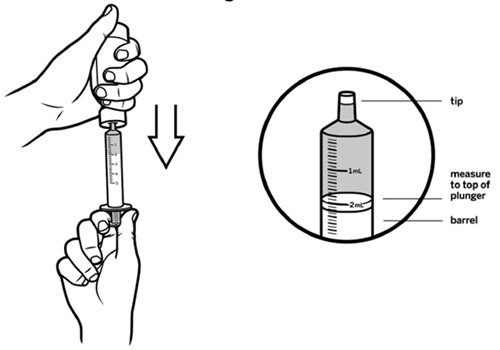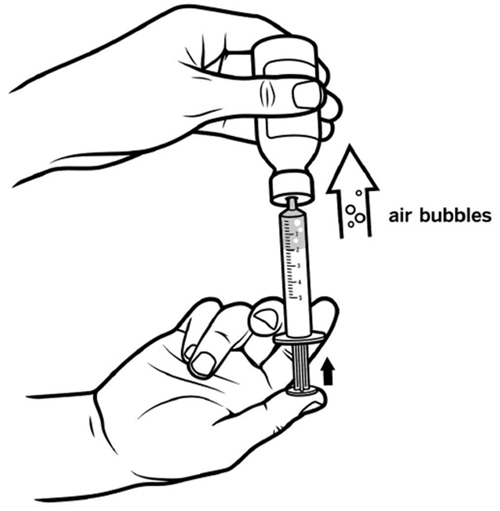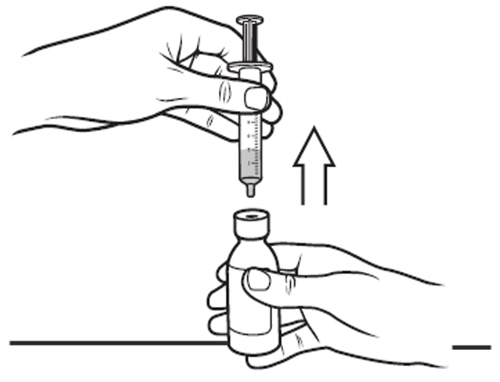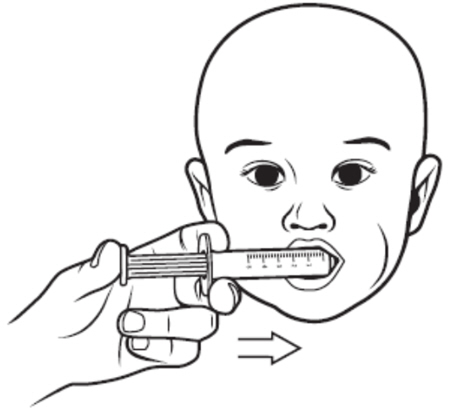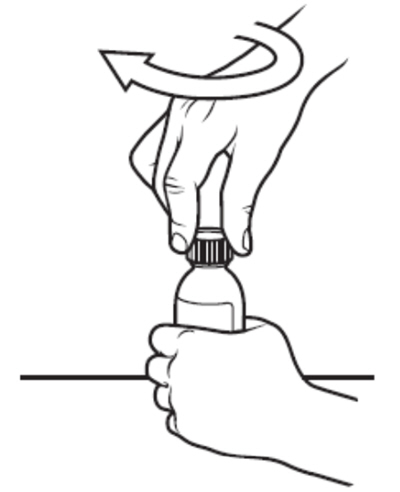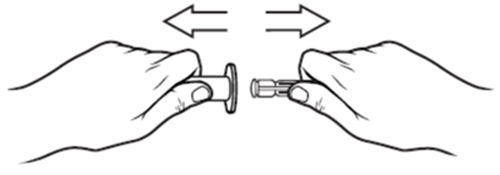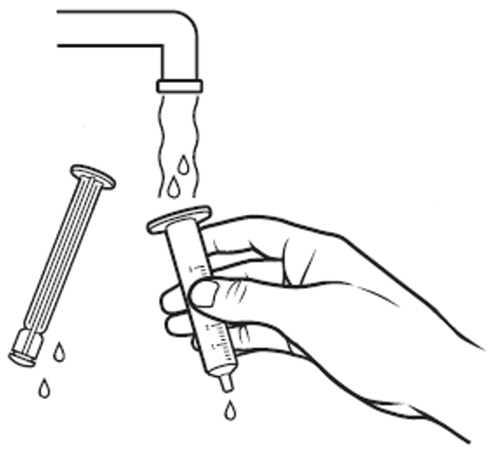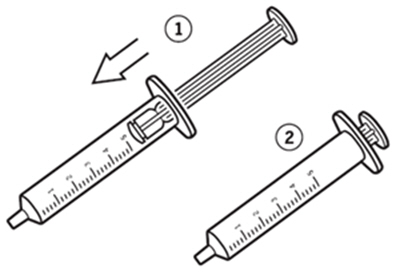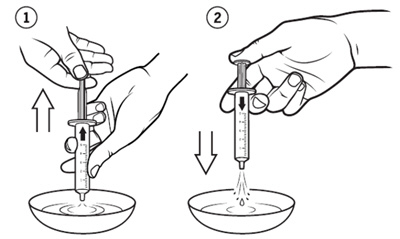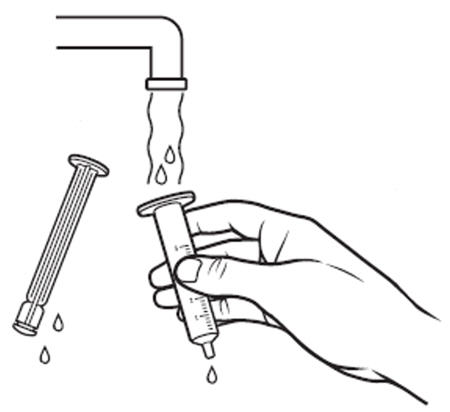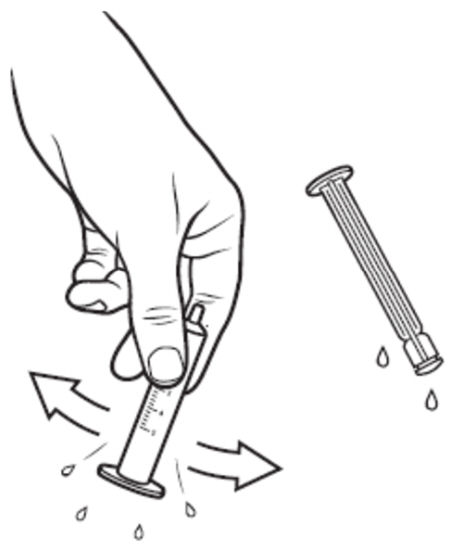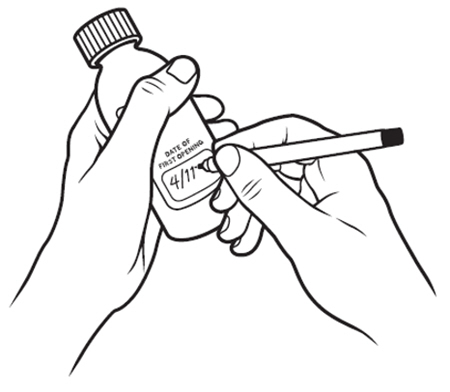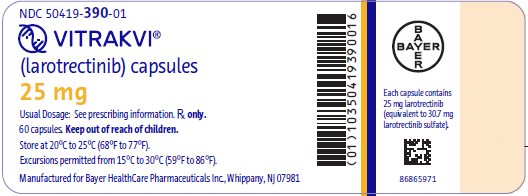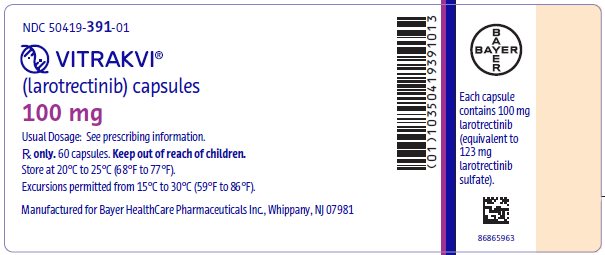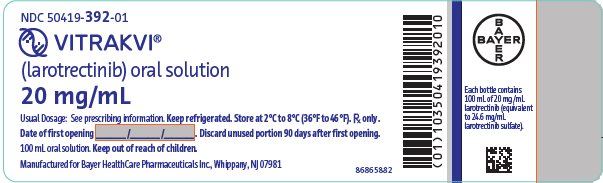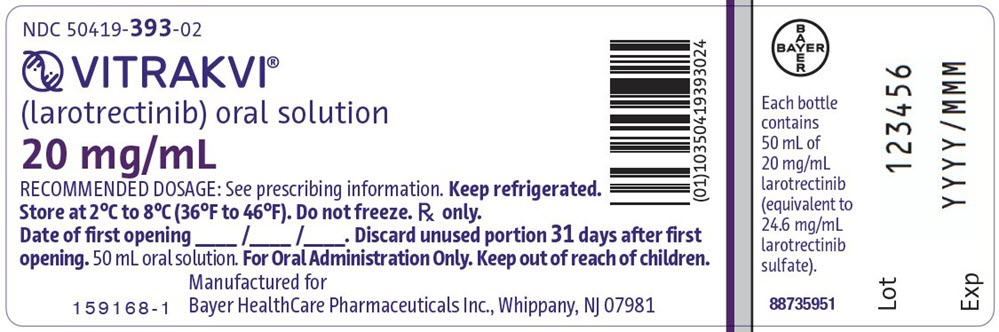 DRUG LABEL: VITRAKVI
NDC: 50419-390 | Form: CAPSULE
Manufacturer: Bayer HealthCare Pharmaceuticals Inc.
Category: prescription | Type: HUMAN PRESCRIPTION DRUG LABEL
Date: 20250430

ACTIVE INGREDIENTS: LAROTRECTINIB 25 mg/1 1
INACTIVE INGREDIENTS: GELATIN, UNSPECIFIED; TITANIUM DIOXIDE

HIGHLIGHTS OF PRESCRIBING INFORMATION

These highlights do not include all the information needed to use VITRAKVI safely and effectively. See full prescribing information for VITRAKVI.
VITRAKVI® (larotrectinib) capsules, for oral use
VITRAKVI® (larotrectinib) oral solution
Initial U.S. Approval: 2018

RECENT MAJOR CHANGES

Indications and Usage (1) | 4/2025
Dosage and Administration (2.1) | 4/2025
Warnings and Precautions (5.1, 5.2, 5.3) | 4/2025

1 INDICATIONS AND USAGE

VITRAKVI is a kinase inhibitor indicated for the treatment of adult and pediatric patients with solid tumors that:

- have a neurotrophic receptor tyrosine kinase (NTRK) gene fusion without a known acquired resistance mutation,
- are metastatic or where surgical resection is likely to result in severe morbidity, and
- have no satisfactory alternative treatments or that have progressed following treatment.

Select patients for therapy based on an FDA-approved test. (1, 2.1)

2 DOSAGE AND ADMINISTRATION

- Select patients for treatment with VITRAKVI based on the presence of a NTRK gene fusion (2.1, 14).
- Recommended Dosage in Adult and Pediatric Patients with Body Surface Area of 1 Meter-Squared or greater: 100 mg orally twice daily (2.2)
- Recommended Dosage in Pediatric Patients with Body Surface Area of Less Than 1 Meter-Squared: 100 mg/m^2 orally twice daily (2.2)

3 DOSAGE FORMS AND STRENGTHS

- Capsules: 25 mg, 100 mg (3)
- Oral Solution: 20 mg/mL (3)

4 CONTRAINDICATIONS

None. (4)

5 WARNINGS AND PRECAUTIONS

- Central Nervous System (CNS) Effects: Advise patients and caretakers of the risk of CNS adverse reactions including dizziness, cognitive impairment, mood disorders, and sleep disturbances. Advise patients not to drive or operate hazardous machinery if experiencing neurotoxicity. Withhold and modify dosage, or permanently discontinue VITRAKVI based on severity. (2.3, 5.1)
- Skeletal Fractures: Promptly evaluate patients with signs or symptoms of fractures. (5.2)
- Hepatotoxicity: Obtain liver function tests (ALT, AST, ALP and bilirubin) before initiation of VITRAKVI and every 2 weeks during the first 2 months of treatment, then monthly thereafter or as clinically indicated. Temporarily withhold, reduce dose, or permanently discontinue VITRAKVI based on severity. (2.4, 5.3)
- Embryo-Fetal Toxicity: Can cause fetal harm. Advise females with reproductive potential of potential risk to the fetus and to use effective contraception. (5.4, 8.3)

6 ADVERSE REACTIONS

The most common (≥ 20%) adverse reactions, including laboratory abnormalities, with VITRAKVI were increased AST, increased ALT, anemia, hypoalbuminemia, musculoskeletal pain, increased alkaline phosphatase, leukopenia, lymphopenia, neutropenia, hypocalcemia, fatigue, vomiting, cough, constipation, pyrexia, diarrhea, nausea, abdominal pain, dizziness, and rash (6).

To report SUSPECTED ADVERSE REACTIONS, contact Bayer HealthCare Pharmaceuticals Inc. at 1-888-842-2937 or FDA at 1-800-FDA-1088 or www.fda.gov/medwatch.

7 DRUG INTERACTIONS

- Strong CYP3A4 Inhibitors: Avoid coadministration of strong CYP3A4 inhibitors with VITRAKVI. If coadministration cannot be avoided, reduce the VITRAKVI dose. (2.5, 7.1)
- Moderate CYP3A4 Inhibitors: Monitor for adverse reactions more frequently in patients coadministered a moderate CYP3A4 inhibitor with VITRAKVI and reduce the VITRAKVI dosage based on severity of adverse reactions. (7.1)
- Strong CYP3A4 Inducers: Avoid coadministration of strong CYP3A4 inducers with VITRAKVI. If coadministration cannot be avoided, increase the VITRAKVI dose. (2.6, 7.1)
- Moderate CYP3A4 Inducers: Increase the VITRAKVI dose. (2.6, 7.1)
- Sensitive CYP3A4 Substrates: Avoid coadministration of sensitive CYP3A4 substrates with VITRAKVI. (7.2)

8 USE IN SPECIFIC POPULATIONS

- Lactation: Advise not to breastfeed. (8.2)
- Hepatic Impairment: Reduce the starting dose of VITRAKVI in patients with moderate (Child-Pugh B) to severe (Child-Pugh C) hepatic impairment. (2.7, 8.7)

FULL PRESCRIBING INFORMATION

1 INDICATIONS AND USAGE

VITRAKVI is indicated for the treatment of adult and pediatric patients with solid tumors that:

- have a neurotrophic receptor tyrosine kinase (NTRK) gene fusion without a known acquired resistance mutation,
- are metastatic or where surgical resection is likely to result in severe morbidity, and
- have no satisfactory alternative treatments or that have progressed following treatment.

Select patients for therapy based on an FDA-approved test [see Dosage and Administration (2.1)].

2 DOSAGE AND ADMINISTRATION

2.1 Patient Selection

Select patients for treatment with VITRAKVI based on the presence of a NTRK gene fusion in tumor specimens [see Clinical Studies (14)].

In patients with secretory breast cancer, mammary analogue secretory cancer (MASC), congenital mesoblastic nephroma (CMN), or infantile fibrosarcoma, consider treatment without confirmation of NTRK rearrangements in tumor specimens.

Information on FDA-approved tests is available at http://www.fda.gov/companiondiagnostics.

2.2 Recommended Dosage

Recommended Dosage in Adult and Pediatric Patients with Body Surface Area of 1 Meter-Squared or greater

The recommended dosage of VITRAKVI is 100 mg orally twice daily, with or without food, until disease progression or until unacceptable toxicity.

Recommended Dosage in Pediatric Patients with Body Surface Area Less Than 1 Meter-Squared

The recommended dosage of VITRAKVI is 100 mg/m^2 orally twice daily, with or without food, until disease progression or until unacceptable toxicity.

2.3 Dosage Modifications for Adverse Reactions

For Grade 2 and higher liver function test abnormalities, refer to Section 2.4, Table 2, Dosage Modifications for Hepatotoxicity.

For all other Grade 3 or 4 adverse reactions:

- Withhold VITRAKVI until adverse reaction resolves or improves to baseline or Grade 1. Resume at the next dosage modification if resolution occurs within 4 weeks.
- Permanently discontinue VITRAKVI if an adverse reaction does not resolve within 4 weeks.

The recommended dosage reductions for VITRAKVI for adverse reactions are provided in Table 1.

Table 1 Recommended Dosage Reductions for VITRAKVI for Adverse Reactions
Dosage Reduction | Adult and Pediatric Patients with Body Surface Area of 1 m^2 or Greater | Pediatric Patients with Body Surface Area Less Than 1 m^2
First | 75 mg orally twice daily | 75 mg/m^2 orally twice daily
Second | 50 mg orally twice daily | 50 mg/m^2 orally twice daily
Third | 100 mg orally once daily | 25 mg/m^2 orally twice daily [Pediatric patients on 25 mg/m^2 orally twice daily should remain on this dosage even if body surface area becomes greater than 1 m^2 during the treatment. Maximum dose should be 25 mg/m^2 orally twice daily at the third dosage modification.]

Permanently discontinue VITRAKVI in patients who are unable to tolerate VITRAKVI after three dose modifications.

2.4 Dosage Modifications for Hepatotoxicity

The recommended dosage modifications for VITRAKVI liver function test abnormalities are provided in Table 2.

For CTCAE Grade 2 ALT and/or AST elevation, monitor liver function frequently as clinically indicated, to establish whether a dose interruption or reduction is required [see Warnings and Precautions (5.3)].

Table 2 Recommended Dosage Modifications for VITRAKVI for Hepatotoxicity
Severity [Grading defined by National Cancer Institute Common Terminology Criteria for Adverse Events (NCI CTCAE) version 4.03] | Dosage Modification
AST or ALT ≥ 5 × ULN with bilirubin ≤ 2 × ULN [see Warnings and Precautions (5.3)] | - Withhold VITRAKVI until recovery to ≤ Grade 1 or return to baseline. - Resume VITRAKVI at the next lower dose level. - Permanently discontinue if a Grade 4 AST and/or ALT elevation occurs after resuming VITRAKVI.
AST or ALT > 3 × ULN with total bilirubin > 2 × ULN in the absence of alternative causes | - Permanently discontinue VITRAKVI.
ALT = alanine aminotransferase; AST = aspartate aminotransferase; ULN = upper limit of normal

2.5 Dosage Modifications for Coadministration with Strong CYP3A4 Inhibitors

Avoid coadministration of strong CYP3A4 inhibitors with VITRAKVI. If coadministration of a strong CYP3A4 inhibitor cannot be avoided, reduce the VITRAKVI dose by 50%. After the inhibitor has been discontinued for 3 to 5 elimination half-lives, resume the VITRAKVI dose that was used prior to initiating the CYP3A4 inhibitor [see Drug Interactions (7.1), Clinical Pharmacology (12.3)].

2.6 Dosage Modifications for Coadministration with Strong or Moderate CYP3A4 Inducers

Avoid coadministration of strong CYP3A4 inducers with VITRAKVI. If coadministration of a strong CYP3A4 inducer cannot be avoided, double the VITRAKVI dose. Additionally, for coadministration with a moderate CYP3A4 inducer, double the VITRAKVI dose. After the inducer has been discontinued for 3 to 5 elimination half-lives, resume the VITRAKVI dose that was used prior to initiating the CYP3A4 inducer [see Drug Interactions (7.1), Clinical Pharmacology (12.3)].

2.7 Dosage Modifications for Patients with Hepatic Impairment

Reduce the starting dose of VITRAKVI by 50% in patients with moderate (Child-Pugh B) to severe (Child-Pugh C) hepatic impairment [see Use in Specific Populations (8.6), Clinical Pharmacology (12.3)].

2.8 Administration

VITRAKVI capsule or oral solution may be used interchangeably.

Do not make up a missed dose within 6 hours of the next scheduled dose.

If vomiting occurs after taking a dose of VITRAKVI, take the next dose at the scheduled time.

Capsules

Swallow capsules whole with water. Do not chew or crush the capsules.

Oral Solution packaged in one bottle containing 100 mL

- Store the glass bottle of VITRAKVI oral solution in the refrigerator. Discard any unused VITRAKVI oral solution remaining after 90 days of first opening the bottle.
- Prior to preparing an oral dose for administration, refer to the Instructions for Use.

Oral Solution packaged in two bottles each containing 50 mL

- Store the glass bottles of VITRAKVI oral solution in the refrigerator. Discard any unused VITRAKVI oral solution remaining after 31 days of first opening the bottle.
- Prior to preparing an oral dose for administration, refer to the Instructions for Use.

3 DOSAGE FORMS AND STRENGTHS

Capsules

- 25 mg: white opaque hard gelatin capsule, size 2, with blue printing of "BAYER" cross and "25 mg" on body of capsules. 25 mg larotrectinib is equivalent to 30.7 mg larotrectinib sulfate.
- 100 mg: white opaque hard gelatin capsule, size 0, with blue printing of "BAYER" cross and "100 mg" on body of capsule. 100 mg larotrectinib is equivalent to 123 mg larotrectinib sulfate.

Oral Solution packaged in one bottle containing 100 mL

- 20 mg/mL: clear yellow to orange solution. 20 mg/mL larotrectinib is equivalent to 24.6 mg/mL larotrectinib sulfate.

Oral Solution packaged in two bottles each containing 50 mL

- 20 mg/mL: colorless to yellow or orange or red or brownish solution. 20 mg/mL larotrectinib is equivalent to 24.6 mg/mL larotrectinib sulfate.

4 CONTRAINDICATIONS

None.

5 WARNINGS AND PRECAUTIONS

5.1 Central Nervous System Effects

Central nervous system (CNS) adverse reactions occurred in patients receiving VITRAKVI, including dizziness, cognitive impairment, mood disorders, and sleep disturbances.

In patients who received VITRAKVI (n=444), all grades CNS effects including cognitive impairment, mood disorders, dizziness and sleep disorders were observed in 40.3% with Grades 3-4 in 3.8% of patients.

Cognitive impairment occurred in 11% of patients. The median time to onset of cognitive impairment was 6 months (range: 2 days to 56 months). Cognitive impairment occurring in ≥ 1% of patients included memory impairment (4.1%), disturbance in attention (3.6%), confusional state (2.3%), cognitive disorder (1.6%), delirium (1.4%), and hallucination (1.1%). Grade 3 cognitive adverse reactions occurred in 1.8% of patients and Grade 4 cognitive adverse reactions in 0.2% of patients. Among the 49 patients with cognitive impairment, 6% required a dose modification, and 18% required dose interruption.

Mood disorders occurred in 14% of patients. The median time to onset of mood disorders was 3.3 months (range: 1 day to 65 months). Mood disorders occurring in ≥ 1% of patients included anxiety (5%), agitation (3.2%), depression (3.2%), irritability (2.3%), and restlessness (1.1%). Grade 3 mood disorders occurred in 0.9% of patients. Among the 63 patients who experienced mood disorders, no patient required a dose modification, and 1.6% required dose interruption.

Dizziness occurred in 22% of patients, and Grade 3 dizziness occurred in 0.9% of patients. Among the 96 patients who experienced dizziness, 6% of patients required a dose modification, and 5% required dose interruption.

Sleep disturbances occurred in 12% of patients. Sleep disturbances included insomnia (9%), somnolence (3.4%), and sleep disorder (0.5%). Grade 3 sleep disturbances occurred in 0.2% of patients. Among the 54 patients who experienced sleep disturbances, no patient required a dose modification, and 3.7% required dose interruption.

Advise patients and caretakers of these risks with VITRAKVI. Advise patients not to drive or operate hazardous machinery if they are experiencing neurologic adverse reactions. Withhold or permanently discontinue VITRAKVI based on the severity. If withheld, modify the VITRAKVI dosage when resumed [see Dosage and Administration (2.3)].

5.2 Skeletal Fractures

Skeletal fractures can occur in patients taking VITRAKVI.

Among 444 patients who received VITRAKVI across clinical trials, fractures occurred in 7% of patients; 6% of 290 adult patients and 10% of 154 pediatric patients. Median time to first fracture was 13 months (range 27 days to 73 months) in patients followed per fracture. The most common fractures were of the rib (1.4%), fibula, foot, or wrist (0.7% each). Most fractures were associated with minimal or moderate trauma. Some fractures were associated with radiologic abnormalities suggestive of local tumor involvement. VITRAKVI treatment was interrupted due to fracture in 1.4% patients.

Promptly evaluate patients with signs or symptoms of potential fracture (e.g., pain, changes in mobility, deformity). There are no data on the effects of VITRAKVI on healing of known fractures or risk of future fractures.

5.3 Hepatotoxicity

Hepatotoxicity including drug-induced liver injury (DILI) has occurred in patients taking VITRAKVI.

In patients who received VITRAKVI (n=444), increased AST of any grade occurred in 62% of patients and increased ALT of any grade occurred in 61%. Grade 3-4 increased AST or ALT occurred in 7% and 8% of patients, respectively [see Adverse Reactions (6.1)]. The median time to onset of increased AST was 1.9 months (range: 4 days to 3.8 years). The median time to onset of increased ALT was 1.9 months (range: 1 day to 4.9 years). Increased AST and ALT leading to dose modifications occurred in 1.6% and 3.2% of patients, respectively. Increased AST or ALT led to permanent discontinuation in 4 (0.9%) patients.

There have been reports from clinical studies and postmarketing cases of Grade ≥ 2 increases in ALT and/or AST with increases in bilirubin ≥ 2 × ULN.

Obtain liver function tests (ALT, AST, ALP and bilirubin) before initiation of VITRAKVI and monitor every 2 weeks during the first 2 months of treatment, then monthly thereafter, or more frequently following the occurrence of Grade 2 or greater AST or ALT elevation. Temporarily withhold, reduce the dose, or permanently discontinue VITRAKVI based on severity [see Dosage and Administration (2.4)].

5.4 Embryo-Fetal Toxicity

Based on literature reports in human subjects with congenital mutations leading to changes in TRK signaling, findings from animal studies, and its mechanism of action, VITRAKVI can cause fetal harm when administered to a pregnant woman. Larotrectinib resulted in malformations in rats and rabbits at maternal exposures that were approximately 11- and 0.7-times, respectively, those observed at the clinical dose of 100 mg twice daily. Advise women of the potential risk to a fetus. Advise females of reproductive potential to use an effective method of contraception during treatment and for 1 week after the last dose of VITRAKVI [see Use in Specific Populations (8.1, 8.3)].

6 ADVERSE REACTIONS

The following clinically significant adverse reactions are described elsewhere in the labeling:

- Central Nervous System Effects [see Warnings and Precautions (5.1)]
- Skeletal Fractures [see Warnings and Precautions (5.2)]
- Hepatotoxicity [see Warnings and Precautions (5.3)]

6.1 Clinical Trial Experience

Because clinical trials are conducted under widely varying conditions, adverse reaction rates observed in the clinical trials of a drug cannot be directly compared to rates in the clinical trials of another drug and may not reflect the rates observed in practice.

Unless noted, data in WARNINGS AND PRECAUTIONS and below reflects exposure to VITRAKVI in 444 patients, including 62% patients exposed for greater than 6 months, 44% patients exposed for greater than 1 year, and 30% patients exposed for greater than 2 years. VITRAKVI was studied in one adult dose-finding trial [LOXO-TRK-14001 (n = 75)], one pediatric dose-finding trial [SCOUT (n = 154)], and one single arm trial [NAVIGATE (n = 215)]. All patients had an unresectable or metastatic solid tumor and no satisfactory alternative treatment options or disease progression following treatment.

Across these 444 patients, the median age was 44 years (range: 18 days to 90 years); 35% were younger than 18 years; 53% were female; 59% were White, 24% were Asian and, 4% were Black; and 7% were Hispanic/Latino. Most adults (91%) received VITRAKVI 100 mg orally twice daily and 91% of pediatrics (< 18 years) received VITRAKVI 100 mg/m^2 twice daily up to a maximum dose of 100 mg twice daily. The dose ranged from 50 mg daily to 200 mg twice daily in adults and 9.6 mg/m^2 twice daily to 120 mg/m^2 twice daily in pediatrics [see Use in Specific Populations (8.4)].

The most common serious adverse reactions (≥ 2%) were pneumonia, pyrexia, and dyspnea. Grade 3 or 4 adverse reactions occurred in 60% of patients; adverse reactions leading to dose interruption or modification occurred in 45% and 11% of patients, respectively, and 12% permanently discontinued VITRAKVI for adverse reactions.

The most common adverse reactions (1% each) that resulted in permanent discontinuation of VITRAKVI were increased ALT and increased AST.

The most common adverse reactions (≥ 3%) resulting in dose interruption were increased ALT (6%), increased AST (5%), neutrophil count decreased (4.7%), pyrexia (4.3%), and vomiting (3.2%). Most (64%) adverse reactions leading to dose interruption occurred during the first three months of exposure.

The most common adverse reactions (≥ 20%), including laboratory abnormalities, in order of decreasing frequency were increased AST, increased ALT, anemia, hypoalbuminemia, musculoskeletal pain, increased alkaline phosphatase, leukopenia, lymphopenia, neutropenia, hypocalcemia, fatigue, vomiting, cough, constipation, pyrexia, diarrhea, nausea, abdominal pain, dizziness, and rash.

Adverse reactions of VITRAKVI occurring in ≥ 10% of patients and laboratory abnormalities worsening from baseline in ≥ 20% of patients are summarized in Table 3 and Table 4, respectively.

Table 3 Adverse Reactions Occurring in ≥ 10% of Patients Treated with VITRAKVI
Adverse Reaction [The adverse reaction identifies a composite term:] | VITRAKVI N = 444
Adverse Reaction [The adverse reaction identifies a composite term:] | All Grades [National Cancer Institute-Common Terminology Criteria for Adverse Events (NCI-CTCAE) v 4.03.] (%) | Grade 3-4 [Grade 4 adverse reaction: 1 of cognitive impairment, 1 of pyrexia.] (%)
Musculoskeletal and Connective Tissue
Musculoskeletal Pain [Includes: arthralgia, back pain, bone pain, flank pain, groin pain, growing pains, musculoskeletal chest pain, musculoskeletal discomfort, musculoskeletal pain, musculoskeletal stiffness, myalgia, neck pain, non-cardiac chest pain, pain in extremity, pain in jaw, and tendon pain] | 41 | 3.6
General
Fatigue [Includes: fatigue, asthenia] | 31 | 2.5
Pyrexia | 26 | 2.3
Edema [Includes: face edema, generalized edema, lip edema, localized edema, edema, edema genital, edema peripheral, periorbital edema, and swelling] | 17 | 0.7
Respiratory, Thoracic and Mediastinal
Cough [Includes: cough, productive cough, and upper-airway cough syndrome] | 29 | 0.5
Dyspnea [Includes: dyspnea, and dyspnea exertional] | 17 | 2.7
Nasal congestion | 10 | 0
Nervous System
Dizziness [Includes: dizziness, dizziness postural, and vertigo] | 22 | 0.9
Headache | 17 | 0.9
Cognitive Impairment [Includes: amnesia, aphasia, cognitive disorder, confusional state, delirium, disturbance in attention, hallucination, hallucination visual, memory impairment, mental impairment, mental status changes] | 11 | 2
Gastrointestinal
Vomiting | 30 | 1.1
Constipation | 27 | 0.5
Diarrhea | 26 | 2.9
Nausea | 25 | 0.5
Abdominal pain [Includes: abdominal discomfort, abdominal pain, abdominal pain lower, abdominal pain upper, abdominal tenderness, epigastric discomfort, and gastrointestinal pain] | 24 | 1.4
Skin and Subcutaneous Tissue Disorders
Rash [Includes: dermatitis, dermatitis acneiform, dermatitis bullous, dermatitis exfoliative generalized, eczema, eczema asteatotic, palmar-plantar erythrodysaesthesia syndrome, rash, rash erythematous, rash macular, rash maculo-papular, rash papular, rash pruritic, and rash pustular] | 21 | 0.2
Psychiatric
Mood disorders [Includes: agitation, anxiety, depression, depressed mood, euphoric mood, fear, feeling jittery, irritability, panic attack, psychomotor hyperactivity, restlessness] | 14 | 0.9
Sleep Disturbance [Includes: insomnia, sleep disorder, somnolence] | 12 | 0.2
Investigations
Increased weight | 17 | 4.1
Metabolism and Nutrition
Decreased appetite | 14 | 1.1
Infections and Infestations
Upper respiratory tract infection | 18 | 0.7
Urinary tract infection [Includes: cystitis, cystitis escherichia, escherichia urinary tract infection, kidney infection, pyelonephritis, pyelonephritis acute, pyelonephritis chronic, and urinary tract infection] | 14 | 1.8
Nasopharyngitis | 11 | 0

Clinically relevant adverse reactions occurring in ≤ 10% of patients include fractures (7%).

Table 4 Laboratory Abnormalities Occurring in ≥ 20% Patients Treated with VITRAKVI
Laboratory Abnormality | VITRAKVI [Based on NCI CTCAE v4.03]
Laboratory Abnormality | All Grades (%) [Denominator for each laboratory parameter is based on the number of patients with a baseline and post-treatment laboratory value available which ranged from 416 to 442 patients.] | Grade 3-4 (%)
Chemistry
Increased AST | 62 | 7
Increased ALT | 61 | 8
Hypoalbuminemia | 44 | 2.7
Increased alkaline phosphatase | 40 | 3
Hypocalcemia | 32 | 3.1
Hematology
Anemia | 45 | 8
Leukopenia | 37 | 3.8
Lymphopenia | 35 | 11
Neutropenia | 34 | 11

7 DRUG INTERACTIONS

7.1 Effects of Other Drugs on VITRAKVI

Strong and Moderate CYP3A4 Inhibitors

Coadministration of VITRAKVI with a strong or moderate CYP3A4 inhibitor may increase larotrectinib plasma concentrations, which may result in a higher incidence of adverse reactions [see Clinical Pharmacology (12.3)]. Avoid coadministration of VITRAKVI with strong CYP3A4 inhibitors, including grapefruit or grapefruit juice. If coadministration of strong CYP3A4 inhibitors cannot be avoided, modify VITRAKVI dose as recommended [see Dosage and Administration (2.5)]. In patients coadministered a moderate CYP3A4 inhibitor with VITRAKVI, monitor for adverse reactions more frequently and reduce the VITRAKVI dosage based on the severity of emergent adverse reactions [see Dosage and Administration (2.3)].

Strong and Moderate CYP3A4 Inducers

Coadministration of VITRAKVI with a strong or moderate CYP3A4 inducer may decrease larotrectinib plasma concentrations, which may decrease the efficacy of VITRAKVI [see Clinical Pharmacology (12.3)]. Avoid coadministration of VITRAKVI with strong CYP3A4 inducers, including St. John's wort. If coadministration of strong CYP3A4 inducers cannot be avoided, modify VITRAKVI dose as recommended. For coadministration with moderate CYP3A4 inducers, modify VITRAKVI dose as recommended [see Dosage and Administration (2.6)].

7.2 Effects of VITRAKVI on Other Drugs

Sensitive CYP3A4 Substrates

Coadministration of VITRAKVI with sensitive CYP3A4 substrates may increase their plasma concentrations, which may increase the incidence or severity of adverse reactions [see Clinical Pharmacology (12.3)]. Avoid coadministration of VITRAKVI with sensitive CYP3A4 substrates. If coadministration of these sensitive CYP3A4 substrates cannot be avoided, monitor patients for increased adverse reactions of these drugs.

8 USE IN SPECIFIC POPULATIONS

8.1 Pregnancy

Risk Summary

Based on literature reports in human subjects with congenital mutations leading to changes in TRK signaling, findings from animal studies, and its mechanism of action [see Clinical Pharmacology (12.1)], VITRAKVI can cause embryo-fetal harm when administered to a pregnant woman. There are no available data on VITRAKVI use in pregnant women. Administration of larotrectinib to pregnant rats and rabbits during the period of organogenesis resulted in malformations at maternal exposures that were approximately 11- and 0.7-times, respectively, those observed at the clinical dose of 100 mg twice daily (see Data). Advise pregnant women of the potential risk to a fetus.

In the U.S. general population, the estimated background risk of major birth defects and miscarriage in clinically recognized pregnancies is 2% to 4% and 15% to 20%, respectively.

Data

Human Data

Published reports of individuals with congenital mutations in TRK pathway proteins suggest that decreases in TRK-mediated signaling are correlated with obesity, developmental delays, cognitive impairment, insensitivity to pain, and anhidrosis.

Animal Data

Larotrectinib crosses the placenta in animals. Larotrectinib did not result in embryolethality at maternally toxic doses [up to 40 times the human exposure based on area under the curve (AUC) at the clinical dose of 100 mg twice daily] in embryo-fetal development studies in pregnant rats dosed during the period of organogenesis; however, larotrectinib was associated with fetal anasarca in rats from dams treated at twice-daily doses of 40 mg/kg [11 times the human exposure (AUC) at the clinical dose of 100 mg twice daily]. In pregnant rabbits, larotrectinib administration was associated with omphalocele at twice-daily doses of 15 mg/kg (0.7 times the human exposure at the clinical dose of 100 mg twice daily).

8.2 Lactation

Risk Summary

There are no data on the presence of larotrectinib or its metabolites in human milk and no data on its effects on the breastfed child or on milk production. Because of the potential for serious adverse reactions in breastfed children, advise women not to breastfeed during treatment with larotrectinib and for 1 week after the last dose.

8.3 Females and Males of Reproductive Potential

Pregnancy Testing

Verify pregnancy status in females of reproductive potential prior to initiating VITRAKVI [see Use in Specific Populations (8.1)].

Contraception

VITRAKVI can cause embryo-fetal harm when administered to a pregnant woman [see Use in Specific Populations (8.1)].

Females

Advise female patients of reproductive potential to use effective contraception during treatment with VITRAKVI and for 1 week after the last dose.

Males

Advise males with female partners of reproductive potential to use effective contraception during treatment with VITRAKVI and for 1 week after the last dose.

Infertility

Females

Based on histopathological findings in the reproductive tracts of female rats in a 1-month repeated-dose study, VITRAKVI may reduce fertility [See Nonclinical Toxicology (13.1)].

8.4 Pediatric Use

The safety and effectiveness of VITRAKVI in pediatric patients was established based upon data from three multicenter, open-label, single-arm clinical trials in adult or pediatric patients. [see Adverse Reactions (6.1), Clinical Studies (14)].

The efficacy of VITRAKVI was evaluated in 131 pediatric patients and is described in the Clinical Studies section [see Clinical Studies (14)]. The safety of VITRAKVI was evaluated in 154 pediatric patients who received VITRAKVI. Of these 154 patients, 31% were <1 month to < 2 years (n = 47), 49% were 2 years to < 12 years (n = 75), and 21% were 12 years to < 18 years (n = 32); 25% had metastatic disease, 44% had locally advanced disease, and 31% had primary CNS; and 82% had received prior treatment for their cancer, including surgery, radiotherapy, or systemic therapy, including radioactive iodine therapy (RAI). The most common cancers were infantile fibrosarcoma (32%), primary CNS tumors (31%), soft tissue sarcoma (27%), and thyroid cancer (4%). The median duration of exposure was 14.8 months (range: 0.4 months to 87.4 months).

Due to the small number of pediatric and adult patients, the single arm design of clinical studies of VITRAKVI, and confounding factors such as differences in susceptibility to infections between pediatric and adult patients, it is not possible to determine whether differences in the incidence of adverse reactions to VITRAKVI are related to patient age or other factors. Adverse reactions occurring more frequently (at least a 10% increase in per-patient incidence) in pediatric patients compared to adult patients were vomiting (51% versus 18%), pyrexia (47% versus 15%), cough (36% versus 23%), diarrhea (34% versus 21%), upper respiratory tract infection (33% versus 10%), headache (25% versus 13%), nasopharyngitis (20% versus 7%), nasal congestion (18% versus 7%), gastroenteritis (13% versus 2%), and rhinitis (12% versus 0%).

Laboratory abnormalities occurring more frequently (at least a 10% increase in per-patient incidence) in pediatric patients compared to adult patients were AST increased (75% versus 55% in adults), ALT increased (69% versus 57% in adults), neutrophil count decrease (59% versus 20% in adults), leukocyte count decrease (46% versus 32% in adults), hyperkalemia (39% versus 16%), glucose decrease (29% versus 13% in adults), and lymphocyte increase (25% versus 1%). Three of the 154 pediatric patients discontinued VITRAKVI due to an adverse reaction associated with a laboratory abnormality (1 patient with Grade 3 increased ALT and 2 patients with Grade 3 decreased neutrophil count).

The pharmacokinetics of VITRAKVI in the pediatric population were similar to those seen in adults [see Clinical Pharmacology (12.3)].

Juvenile Animal Toxicity Data

Larotrectinib was administered in a juvenile toxicity study in rats at twice daily doses of 0.2, 2 and 7.5 mg/kg from postnatal day (PND) 7 to 27 and at twice daily doses of 0.6, 6 and 22.5mg/kg between PND 28 and 70. The dosing period was equivalent to human pediatric populations from newborn to adulthood. The doses of 2/6 mg/kg twice daily [approximately 0.7 times the human exposure (AUC) at the clinical dose of 100 mg twice daily] and 7.5/22.5 mg/kg twice daily (approximately 4 times the human exposure at the clinical dose of 100 mg twice daily) resulted in mortality between PND 9 to 99; a definitive cause of death was not identified in the majority of cases.

The main findings were transient central nervous system-related signs including head flick, tremor, and circling in both sexes. An increase in the number of errors in a maze swim test occurred in females at exposures of approximately 4 times the human exposure (AUC) at the clinical dose of 100 mg twice daily. Decreased growth and delays in sexual development occurred in the mid- and high-dose groups. Mating was normal in treated animals, but a reduction in pregnancy rate occurred at the high-dose of 7.5/22.5 mg/kg twice daily (approximately 4 times the human exposure at the clinical dose of 100 mg twice daily).

8.5 Geriatric Use

Of 444 patients in the overall safety population who received VITRAKVI, 20% of patients were ≥ 65 years of age and 6% of patients were ≥ 75 years of age. No overall differences in safety or effectiveness of VITRAKVI were observed between patients 65 years and older and younger adult patients.

8.6 Hepatic Impairment

No dose adjustment is recommended for patients with mild hepatic impairment (Child-Pugh A). Larotrectinib clearance was reduced in subjects with moderate (Child-Pugh B) to severe (Child-Pugh C) hepatic impairment [see Clinical Pharmacology (12.3)]. Reduce VITRAKVI dose as recommended [see Dosage and Administration (2.7)].

8.7 Renal Impairment

No dose adjustment is recommended for patients with renal impairment of any severity [see Clinical Pharmacology (12.3)].

11 DESCRIPTION

Larotrectinib is a kinase inhibitor. VITRAKVI (larotrectinib) capsules and oral solution are formulated using larotrectinib sulfate. The molecular formula for larotrectinib sulfate is C21H24F2N6O6S and the molecular weight is 526.51 g/mol for the sulfate salt and 428.44 g/mol for the free base. The chemical name is (3S)-N-{5-[(2R)-2-(2,5-difluorophenyl)-1-pyrrolidinyl]pyrazolo[1,5-a]pyrimidin-3-yl}-3-hydroxy-1-pyrrolidinecarboxamide sulfate. Larotrectinib sulfate has the following chemical structure:

Larotrectinib sulfate is an off-white to pinkish yellow solid that is not hygroscopic. The aqueous solubility of larotrectinib at 37°C is pH dependent (very soluble at pH 1.0 and freely soluble at pH 6.8, according to USP descriptive terms of solubility).

VITRAKVI (larotrectinib) capsules and oral solution are for oral use. Each capsule contains 25 mg or 100 mg larotrectinib (30.7 mg and 123 mg larotrectinib sulfate, respectively) in a hard gelatin capsule. The capsule is composed of gelatin, titanium dioxide, and edible ink.

The oral solution packaged in one bottle containing 100 mL contains 20 mg/mL larotrectinib (24.6 mg/mL larotrectinib sulfate) and the following inactive ingredients: purified water, hydroxypropyl betadex, sucrose, glycerin, sorbitol, citric acid, sodium phosphate, sodium citrate dihydrate, propylene glycol and flavoring. Preserved with methylparaben and potassium sorbate.

The oral solution packaged in two bottles each containing 50 mL contains 20 mg/mL larotrectinib (24.6 mg/mL larotrectinib sulfate) and the following inactive ingredients: purified water, hydroxypropyl betadex, sucralose, sodium citrate, strawberry flavor, and citric acid. Preserved with sodium benzoate.

12 CLINICAL PHARMACOLOGY

12.1 Mechanism of Action

Larotrectinib is an inhibitor of the tropomyosin receptor kinases (TRK), TRKA, TRKB, and TRKC. In a broad panel of purified enzyme assays, larotrectinib inhibited TRKA, TRKB, and TRKC with IC50 values between 5-11 nM. One other kinase TNK2 was inhibited at approximately 100-fold higher concentration. TRKA, B, and C are encoded by the genes NTRK1, NTRK2, and NTRK3. Chromosomal rearrangements involving in-frame fusions of these genes with various partners can result in constitutively-activated chimeric TRK fusion proteins that can act as an oncogenic driver, promoting cell proliferation and survival in tumor cell lines.

In in vitro and in vivo tumor models, larotrectinib demonstrated anti-tumor activity in cells with constitutive activation of TRK proteins resulting from gene fusions, deletion of a protein regulatory domain, or in cells with TRK protein overexpression. Larotrectinib had minimal activity in cell lines with point mutations in the TRKA kinase domain, including the clinically identified acquired resistance mutation, G595R. Point mutations in the TRKC kinase domain with clinically identified acquired resistance to larotrectinib include G623R, G696A, and F617L.

12.2 Pharmacodynamics

Cardiac Electrophysiology

At a dose 9-fold higher than the recommended adult dose, VITRAKVI does not prolong QTc intervals to any clinically relevant extent.

12.3 Pharmacokinetics

The pharmacokinetics of larotrectinib were studied in healthy subjects and adult and pediatric patients with locally advanced or metastatic solid tumors. In healthy subjects who received a single dose of VITRAKVI capsules, systemic exposure (Cmax and AUC) of larotrectinib was dose proportional over the dose range of 100 mg to 400 mg (1 to 4 times the recommended adult dose) and slightly greater than proportional at doses of 600 mg to 900 mg (6 to 9 times the recommended adult dose). In adult patients who received VITRAKVI capsules 100 mg twice daily in Study LOXO-TRK-14001, peak plasma levels (Cmax) of larotrectinib were achieved at approximately 1 hour after dosing and steady-state was reached within 3 days. Mean steady-state larotrectinib [coefficient of variation (CV%)] for Cmax was 788 (81%) ng/mL and AUC0-24hr was 4351 (97%) ng*h/mL.

Absorption

The mean absolute bioavailability of VITRAKVI capsules was 34% (range: 32% to 37%). In healthy subjects, the AUC of VITRAKVI oral solution was similar to that of the capsules and the Cmax was 36% higher with the oral solution.

Effect of Food

The AUC of larotrectinib was similar and the Cmax was reduced by 35% after oral administration of a single 100 mg capsule of VITRAKVI to healthy subjects taken with a high-fat meal (approximately 900 calories, 58 grams carbohydrate, 56 grams fat and 43 grams protein) compared to the Cmax and AUC in the fasted state.

Distribution

The mean (CV%) volume of distribution (Vss) of larotrectinib is 48 (38%) L following intravenous administration of larotrectinib in healthy subjects.

Larotrectinib is 70% bound to human plasma proteins in vitro and binding is independent of drug concentrations. The blood-to-plasma concentration ratio is 0.9.

Elimination

The mean (CV%) clearance (CL/F) of larotrectinib is 98 (44%) L/h and the half-life is 2.9 hours following oral administration of VITRAKVI in healthy subjects.

Metabolism

Larotrectinib is metabolized predominantly by CYP3A4. Following oral administration of a single [^14C] radiolabeled 100 mg dose of larotrectinib to healthy subjects, unchanged larotrectinib constituted 19% and an O-linked glucuronide constituted 26% of the major circulating radioactive drug components in plasma.

Excretion

Following oral administration of a single [^14C] radiolabeled 100 mg dose of larotrectinib to healthy subjects, 58% (5% unchanged) of the administered radioactivity was recovered in feces and 39% (20% unchanged) was recovered in urine.

Specific Populations

Age (range: 28 days to 82 years), sex, and body weight (range: 3.8 kg to 179 kg) had no clinically meaningful effect on the pharmacokinetics of larotrectinib.

Pediatric Patients

In pediatric patients, the larotrectinib geometric mean (%CV) AUC0-24hr by age subgroup was: 3348 (66%) ng*h/mL in patients 1 month to < 2 years (n = 9), 4135 (36%) ng*h/mL in patients 2 to < 12 years (n = 15), and 3108 (69%) ng*h/mL and in patients 12 to < 18 years (n = 9).

Patients with Renal Impairment

Following oral administration of a single 100 mg dose of VITRAKVI capsules in subjects with end-stage renal disease (e.g., subjects who required dialysis), the AUC0-INF of larotrectinib increased 1.5-fold and Cmax increased 1.3-fold as compared to that in subjects with normal renal function (creatinine clearance ≥ 90 mL/min as estimated by Cockcroft-Gault). The pharmacokinetics of VITRAKVI in patients with moderate to severe renal impairment (creatinine clearance ≤ 60 mL/min) have not been studied.

Patients with Hepatic Impairment

Following oral administration of a single 100 mg dose of VITRAKVI capsules, the AUC0-INF of larotrectinib increased 1.3-fold in subjects with mild hepatic impairment (Child-Pugh A), 2-fold in subjects with moderate hepatic impairment (Child-Pugh B) and 3.2-fold in subjects with severe hepatic impairment (Child-Pugh C) as compared to that in subjects with normal hepatic function. The Cmax was similar in subjects with mild and moderate hepatic impairment and the Cmax of larotrectinib increased 1.5-fold in subjects with severe hepatic impairment as compared to that in subjects with normal hepatic function [see Dosage and Administration (2.7), Use in Specific Populations (8.6)].

Drug Interaction Studies

Clinical Studies

Effect of CYP3A Inhibitors: Coadministration of a single 100 mg dose of VITRAKVI capsules with itraconazole (strong CYP3A inhibitor) increased the AUC0-INF of larotrectinib by 4.3-fold and the Cmax by 2.8-fold as compared to VITRAKVI administered alone [see Dosage and Administration (2.5), Drug Interactions (7.1)].

Coadministration of VITRAKVI with fluconazole (moderate CYP3A4 inhibitor) is predicted to increase VITRAKVI steady state AUC by 2.7-fold and Cmax by 1.9-fold.

Effect of CYP3A Inducers: Coadministration of a single 100 mg dose of VITRAKVI capsules with rifampin (strong CYP3A inducer) decreased the AUC0-INF of larotrectinib by 81% and the Cmax by 71% as compared to VITRAKVI administered alone [see Dosage and Administration (2.6), Drug Interactions (7.1)].

Coadministration of VITRAKVI with efavirenz (moderate CYP3A4 inducer) is predicted to decrease steady state AUC of VITRAKVI by approximately 72% and Cmax by 60% compared to VITRAKVI administered alone [see Dosage and Administration (2.6), Drug Interactions (7.1)].

Effect of Strong P-glycoprotein (P-gp) Inhibitors: Coadministration of a single 100 mg dose of VITRAKVI capsules with a P-gp inhibitor (rifampin) increased the AUC0-INF of larotrectinib by 1.7-fold and the Cmax by 1.8-fold as compared to VITRAKVI administered alone.

Effect of Larotrectinib on CYP3A4 Substrates: Coadministration of VITRAKVI capsules 100 mg twice daily with a sensitive CYP3A4 substrate (midazolam) increased both the AUC0-INF and Cmax of midazolam by 1.7-fold as compared to midazolam administered alone. The AUC0-INF and Cmax of 1-hydroxymidazolam, the main metabolite of midazolam, were both increased 1.4-fold as compared to when midazolam was administered alone [see Drug Interactions (7.2)].

In Vitro Studies

Effect of Transporter on Larotrectinib: Larotrectinib is a substrate for P-gp and BCRP. Larotrectinib is not a substrate of OAT1, OAT3, OCT1, OCT2, OATP1B1, or OATP1B3.

Effect of Larotrectinib on Transporters: Larotrectinib is not an inhibitor of BCRP, P-gp, OAT1, OAT3, OCT1, OCT2, OATP1B1, OATP1B3, BSEP, MATE1 and MATE2-K at clinically relevant concentrations.

Effect of Larotrectinib on CYP Substrates: Larotrectinib is not an inhibitor or inducer of CYP1A2, CYP2B6, CYP2C8, CYP2C9, CYP2C19, or CYP2D6 at clinically relevant concentrations.

13 NONCLINICAL TOXICOLOGY

13.1 Carcinogenesis, Mutagenesis, Impairment of Fertility

Carcinogenicity studies have not been conducted with larotrectinib. Larotrectinib was not mutagenic in the in vitro bacterial reverse mutation (Ames) assays, with or without metabolic activation, or in the in vitro mammalian mutagenesis assays, with or without metabolic activation. In vivo, larotrectinib was negative in the mouse micronucleus test.

Fertility studies with larotrectinib have not been conducted. In a 3-month repeat-dose toxicity study in the rat, larotrectinib had no effects on spermatogenesis at 75 mg/kg/day (approximately 7 times the human exposure at the 100 mg twice daily dose). Additionally, larotrectinib had no histological effects on the male reproductive tract in rats or monkeys at doses resulting in exposures up to 10 times the human exposure (AUC0-24hr) at the 100 mg twice daily clinical dose.

In a 1-month repeat-dose study in the rat, decreased uterine weight and uterine atrophy were seen at 200 mg/kg/day [approximately 45 times the human exposure (AUC) at the 100 mg twice daily dose]. Fewer corpora lutea and increased incidence of anestrus were also noted at doses ≥ 60 mg/kg/day (approximately 10 times the human exposure at the 100 mg twice daily dose). Decreased fertility occurred in a juvenile animal study [see Use in Specific Populations (8.4)]. There were no findings in female reproductive organs in repeat-dose studies in monkeys at exposures up to 22 times the human exposure at the 100 mg twice daily dose.

13.2 Animal Toxicology and/or Pharmacology

In general toxicology studies conducted in rats and monkeys and in reproductive toxicology studies conducted in rats and rabbits, administration of larotrectinib led to increased food consumption and increased body weight at doses resulting in exposures 0.6 times the human exposure at the 100 mg twice daily clinical dose. Obesity has also been one phenotypic outcome of some human syndromes resulting from congenital mutations in NTRK2 resulting in altered TRK signaling.

14 CLINICAL STUDIES

The efficacy of VITRAKVI was evaluated in pediatric and adult patients with unresectable or metastatic solid tumors with a NTRK gene fusion enrolled in one of three multicenter, open-label, single-arm clinical trials: Study LOXO-TRK-14001 (NCT02122913), SCOUT (NCT02637687), and NAVIGATE (NCT02576431). All patients were required to have progressed following systemic therapy for their disease, if available, or would have required surgery with significant morbidity for locally advanced disease.

Adult patients received VITRAKVI 100 mg orally twice daily and pediatric patients (18 years or younger) received VITRAKVI 100 mg/m^2 up to a maximum dose of 100 mg orally twice daily until unacceptable toxicity or disease progression. Identification of positive NTRK gene fusion status was prospectively determined in local laboratories using next generation sequencing (NGS) (89%), fluorescence in situ hybridization (FISH) or reverse transcription polymerase chain reaction (RT-PCR). NTRK gene fusions were inferred in 14 patients who had a documented ETV6 or NTRK 3 translocation identified by FISH. The major efficacy outcome measures were overall response rate (ORR) and duration of response (DOR), as determined by a blinded independent review committee (BIRC) according to RECIST v1.1.

The assessment of efficacy was based on 339 patients with solid tumors with an NTRK gene fusion enrolled across the three clinical trials. Baseline characteristics were: median age 38 years (range: 18 days to 90 years); 39% <18 years of age; 51% female; 57% White, 28% Asian, 2.4% Black or African American; 6% Hispanic or Latino and ECOG performance status (PS) 0-1 (88%) or 2 (10%). Sixty-three percent of patients had metastatic disease, including patients with brain metastases, and 22% had locally advanced, unresectable disease. Ninety-two percent of patients had received prior treatment for their cancer, including surgery, radiotherapy, or systemic therapy, including RAI. Seventy percent of all patients had received prior systemic therapy in the unresectable or metastatic setting excluding RAI; 30% were treatment naive, 33% had received 1 prior therapy and 37% percent had received 2 or more prior therapies with a median of one prior systemic regimen.

Efficacy results are summarized in Tables 5, 6, and 7.

Table 5 Efficacy Results for Patients with Solid Tumors Harboring NTRK Gene Fusions
Efficacy Parameter | VITRAKVI N = 339
Overall response rate (95% CI) | 60% (55%, 65%)
Complete response rate | 24% [5% were pathological complete response. Patients undergoing a surgical resection whose post-operative pathologic assessment showed no viable tumor cells and negative margins were pathological complete responders provided that no other sites of disease were present.]
Partial response rate | 36%
Duration of response (DOR) | N = 204
Median (months) (95% CI) | 43.3 [Kaplan-Meier estimates] (32.5, NE [NE: Not evaluable])
Range (months) | 0.0+, 73.7+
% with Observed DOR> 12 months | 64%
% with Observed DOR> 24 months | 45%
+ Denotes ongoing response.

Table 6 Efficacy Results by Tumor Type
Tumor Type | Patients (N=339) | ORR |  | DOR Range (months)
Tumor Type | Patients (N=339) | % | 95% CI | DOR Range (months)
Soft tissue sarcoma | 70 | 70% | (58%, 80%) | 0.0+, 72.7+
Infantile fibrosarcoma | 49 | 94% | (83%, 99%) | 1.6+, 73.7+
Primary CNS | 49 | 27% | (15%, 41%) | 1.9+, 57.5+
Lung | 30 | 70% | (51%, 85%) | 1.9+, 56.2+
Thyroid | 30 | 63% | (44%, 80%) | 3.7, 72.4+
Differentiated | 23 | 78% | (56%, 93%) | 4.9, 72.4+
Non-differentiated | 7 | 14% | (0%, 58%) | 3.7 [Observed values at data cutoff, not a range.]
Salivary gland | 25 | 84% | (64%, 95%) | 7.4, 65.2+
MASC | 14 | 79% | (49%, 95%) | 7.7, 59.1
Colorectal [Colorectal Tumor Type includes 23 colon cancers and 1 rectal cancer.] | 24 | 46% | (26%, 67%) | 3.9, 45.2+
Breast | 14 | 57% | (29%, 82%) | 7.4, 58.2+
Secretory | 6 | 83% | (36%, 100%) | 11.1, 58.2+
Non-secretory | 8 | 38% | (9%, 76%) | 7.4, 12.5+
Melanoma | 11 | 45% | (17%, 77%) | 1.9+, 23.2+
Pancreas | 7 | 14% | (0%, 58%) | 5.8
Gastrointestinal stromal tumor | 5 | 80% | (28%, 99%) | 9.5, 50.4+
Cholangiocarcinoma | 4 | 2 SD, 2 NE | NA | NA
Bone sarcoma | 3 | 33% | (1%, 91%) | 9.5
Gastric | 3 | 2 PD, NE | NA | NA
Cancer of unknown primary | 2 | 100% | (16%, 100%) | 5.6, 7.4
Congenital mesoblastic nephroma | 2 | 100% | (16%, 100%) | 32.9, 44.5
Prostate | 2 | SD, PD | NA | NA
Appendix | 1 | SD | NA | NA
Cervix | 1 | SD | NA | NA
Duodenal | 1 | PD | NA | NA
Esophageal | 1 | PD | NA | NA
External auditory canal | 1 | 100% | (3%, 100%) | 33.8+
Hepatic | 1 | NE | NA | NA
Thymus | 1 | PD | NA | NA
Urothelial | 1 | PD | NA | NA
Uterus | 1 | NE | NA | NA
NA = not applicable due to small numbers or lack of response; NE = not evaluable; SD = stable disease; PD = progressive disease.
+ Denotes ongoing response.

The ORR for patients with NTRK1 fusions (n=142) was 59% (95% CI: 51, 67), NTRK2 fusions (n=44) was 32% (95% CI: 19, 48) and NTRK3 fusions (n=142) was 67% (95% CI: 59, 75).

Table 7 Efficacy Results by NTRK Fusion Partner
NTRK Partner [Includes fusion partners which are represented by 3 or more patients in the efficacy analysis set. Does not represent all potential fusion partners.] | Patients (N=339) | ORR |  | DOR Range (months)
NTRK Partner [Includes fusion partners which are represented by 3 or more patients in the efficacy analysis set. Does not represent all potential fusion partners.] | Patients (N=339) | % | 95% CI | DOR Range (months)
ETV6-NTRK3 | 102 | 80% | (71%, 88%) | 0.0+, 66.7+
TPM3-NTRK1 | 63 | 67% | (54%, 78%) | 0.8+, 73.7+
LMNA-NTRK1 | 29 | 69% | (49%, 85%) | 3.4, 70.7+
Inferred ETV6-NTRK3 | 14 | 93% | (66%, 100%) | 1.6+, 73.4+
TPR-NTRK1 | 10 | 60% | (26%, 88%) | 3.0+, 38.7+
EML4-NTRK3 | 6 | 50% | (12%, 88%) | 7.9, 40.7+
IRF2BP2-NTRK1 | 4 | 100% | (40%, 100%) | 3.7, 47.8+
BCR-NTRK2 | 3 | 67% | (9%, 99%) | 9.2+, 11.0
GKAP1-NTRK2 | 3 | 2 SD, 1 PD | NA | NA
NACC2-NTRK2 | 3 | 33% | (1%, 91%) | 3.7 [Observed values at data cutoff, not a range.]
RBPMS-NTRK3 | 3 | 67% | (9%, 99%) | 3.3+, 23.0
SQSTM1-NTRK1 | 3 | 67% | (9%, 99%) | 9.9, 12.9+
PD = progressive disease; SD = stable disease; NA = not applicable.
+ Denotes ongoing response.

16 HOW SUPPLIED/STORAGE AND HANDLING

Capsules

25 mg: Hard gelatin opaque white capsule size #2 with blue printing of "BAYER" cross and "25 mg" on the body of the capsule.

- 60 count bottle | NDC# 50419-390-01

100 mg: Hard gelatin opaque white capsule size #0 with blue printing of "BAYER" cross and "100 mg" on the body of the capsule.

- 60 count bottle | NDC# 50419-391-01

STORAGE AND HANDLING

Store capsules at room temperature 20°C to 25°C (68°F to 77°F); temperature excursions between 15°C and 30°C (59°F to 86°F) are permitted [see USP Controlled Room Temperature].

Oral Solution Packaged in One Bottle Containing 100 mL

20 mg/mL: Clear yellow to orange solution.

- One bottle containing 100 mL | NDC# 50419-392-01

Refrigerate oral solution at 2°C to 8°C (36°F to 46°F). Do not freeze.

Oral Solution Packaged in Two Bottles Each Containing 50 mL

20 mg/mL: Colorless to yellow or orange or red or brownish solution.

- Two bottles each containing 50 mL | NDC# 50419-393-03

Refrigerate oral solution at 2°C to 8°C (36°F to 46°F). Do not freeze.

17 PATIENT COUNSELING INFORMATION

Advise the patient to read the FDA-approved patient labeling (Patient Information and Instructions for Use).

Central Nervous System Effects

Advise patients to notify their healthcare provider if they experience new or worsening neurotoxicity. Advise patients not to drive or operate hazardous machinery if they are experiencing neurologic adverse reactions [see Warnings and Precautions (5.1)].

Skeletal Fractures

Inform patients that bone fractures can occur in patients taking VITRAKVI. Advise patients to report symptoms such as pain, changes in mobility, or deformity to their healthcare provider [see Warnings and Precautions (5.2)].

Hepatotoxicity

Advise patients that they will need to undergo laboratory tests to monitor liver function [see Warnings and Precautions (5.3)].

Embryo-Fetal Toxicity

Advise males and females of reproductive potential of the potential risk to a fetus [see Warnings and Precautions (5.4), Use in Specific Populations (8.1)].

Advise females of reproductive potential to inform their healthcare provider of a known or suspected pregnancy and to use effective contraception during the treatment with VITRAKVI and for 1 week after the last dose [see Use in Specific Populations (8.3)].

Advise males with female partners of reproductive potential to use effective contraception during treatment with VITRAKVI and for 1 week after the last dose [see Use in Specific Populations (8.3)].

Lactation

Advise women not to breastfeed during treatment with VITRAKVI and for 1 week following the last dose [see Use in Specific Populations (8.2)].

Infertility

Advise females of reproductive potential that VITRAKVI may impair fertility [See Nonclinical Toxicology (13.1)].

Drug Interactions

Advise patients and caregivers to inform their healthcare provider of all concomitant medications, including prescription medicines, over-the-counter drugs, vitamins, and herbal products. Inform patients to avoid St. John's wort, grapefruit or grapefruit juice while taking VITRAKVI [see Drug Interactions (7.1, 7.2)].

Manufactured for Bayer HealthCare Pharmaceuticals Inc., Whippany, NJ 07981

PATIENT INFORMATION

VITRAKVI (vi trak vee)
(larotrectinib)
capsules

VITRAKVI (vi trak vee)
(larotrectinib)
oral solution

What is VITRAKVI?
VITRAKVI is a prescription medicine that is used to treat adults and children with solid tumors (cancer) that:

- are caused by certain abnormal neurotrophic receptor tyrosine kinase (NTRK) genes and
- have spread or if surgery to remove their cancer is likely to cause severe complications, and
- there is no acceptable treatment option or the cancer grew or spread on other treatment.

Your healthcare provider will perform a test to make sure that VITRAKVI is right for you.

Before taking VITRAKVI, tell your healthcare provider about all of your medical conditions, including if you:

- have liver problems
- have nervous system (neurological) problems

- are pregnant or plan to become pregnant. VITRAKVI can harm your unborn baby. Tell your healthcare provider right away if you become pregnant during treatment with VITRAKVI or think you may be pregnant.
  Females who are able to become pregnant:
  - Your healthcare provider may do a pregnancy test before you start treatment with VITRAKVI.
  - You should use effective birth control (contraception) during treatment and for 1 week after the last dose of VITRAKVI. Talk to your healthcare provider about birth control methods that may be right for you.
  Males with female partners who are able to become pregnant:
  - You should use effective birth control during treatment with VITRAKVI and for 1 week after the last dose of VITRAKVI.
- are breastfeeding or plan to breastfeed. It is not known if VITRAKVI passes into your breast milk. Do not breastfeed during treatment and for 1 week after the last dose of VITRAKVI.

Tell your healthcare provider about all the medicines you take, including prescription and over-the-counter medicines, vitamins, and herbal supplements.
Taking VITRAKVI with certain other medicines may affect the amount of VITRAKVI or other medicines in your blood and may cause side effects or affect the way that VITRAKVI works.
Know the medicines you take. Keep a list of them to show your healthcare provider and pharmacist when you get a new medicine.

How should I take VITRAKVI?

- Take VITRAKVI exactly as your healthcare provider tells you.
- Do not change your dose or stop taking VITRAKVI unless your healthcare provider tells you.
- VITRAKVI comes in capsules and as an oral solution.
- If your healthcare provider prescribes VITRAKVI oral solution:
  - Your healthcare provider will provide you with the VITRAKVI oral solution, oral syringes and bottle adaptors or send you to a pharmacy that can provide you with VITRAKVI oral solution, oral syringes and bottle adaptors.
  - Your healthcare provider should show you how to correctly measure and give a dose of VITRAKVI oral solution.
  - See the detailed Instructions for Use that comes with VITRAKVI oral solution for information about the correct way to measure and give a dose of VITRAKVI oral solution. If you have any questions, talk to your healthcare provider or pharmacist.
- VITRAKVI is usually taken by mouth 2 times a day.
- Swallow VITRAKVI capsules whole with water. Do not chew or crush the capsules.
- Take VITRAKVI with or without food.
- If you vomit after taking a dose of VITRAKVI, wait and take the next dose at your scheduled time.
- If you miss a dose of VITRAKVI, take it as soon as you remember. If your next scheduled dose is due within 6 hours, skip the missed dose and take your next dose at your regularly scheduled time.
- If you take too much VITRAKVI, call your healthcare provider or go to the nearest hospital emergency room right away.

What should I avoid while taking VITRAKVI?

- VITRAKVI can make you feel dizzy. Do not drive or operate machinery until you know how VITRAKVI affects you.
- Avoid taking St. John's wort, eating grapefruit, or drinking grapefruit juice during treatment with VITRAKVI.

What are the possible side effects of VITRAKVI?
VITRAKVI may cause serious side effects, including:

- Central nervous system (CNS) problems. VITRAKVI may cause dizziness, confusion, problems with concentration, attention, and memory, changes in your mood, and sleep problems. Tell your healthcare provider if you develop any of these symptoms or they get worse.
- Bone fractures. Bone fractures can happen with VITRAKVI. Tell your healthcare provider if you develop pain, changes in your ability to move around, or bone abnormalities.
- Liver problems. Abnormal liver blood tests may occur with VITRAKVI and can sometimes become serious. Your healthcare provider will do blood tests to check your liver function before starting and during treatment with VITRAKVI as needed. Tell your healthcare provider right away if you develop new or worsening symptoms of liver problems including:

- yellowing of your skin or the white part of your eyes (jaundice)
- dark or brown urine
- pain in the upper right side of your stomach area (abdomen)

- bruising or bleeding more easily than normal
- tiredness
- nausea or vomiting
- loss of appetite

Your healthcare provider may decrease your dose, temporarily stop or permanently stop your treatment with VITRAKVI if you develop serious side effects.
The most common side effects of VITRAKVI include:

- increase in certain liver blood tests
- low red blood cell and white blood cell counts
- low levels of protein called albumin in the blood
- muscle and bone pain
- increased levels of enzyme called alkaline phosphatase in the blood (test for liver or bone problems)
- low levels of calcium in the blood
- tiredness
- vomiting

- cough
- constipation
- fever
- diarrhea
- nausea
- stomach (abdomen) pain
- dizziness
- rash

VITRAKVI may affect fertility in females and may affect your ability to become pregnant. Talk to your healthcare provider if this is a concern for you.
These are not all the possible side effects with VITRAKVI. Call your doctor for medical advice about side effects. You may report side effects to FDA at 1-800-FDA-1088.

How should I store VITRAKVI?

- Store VITRAKVI capsules at room temperature between 68˚F to 77˚F (20˚C to 25˚C).
- Store VITRAKVI oral solution in the refrigerator between 36° F to 46° F (2° C to 8° C). Do not freeze.
- Throw away (dispose of) any unused VITRAKVI oral solution:
  - Bottle of 100 mL: remaining 90 days after first opening the bottle
  - Bottle of 50 mL: remaining 31 days after first opening the bottle

Keep VITRAKVI and all medicines out of the reach of children.

General information about the safe and effective use of VITRAKVI.
Medicines are sometimes prescribed for purposes other than those listed in a Patient Information leaflet. Do not use VITRAKVI for a condition for which it was not prescribed. Do not give VITRAKVI to other people, even if they have the same symptoms that you have. It may harm them. You can ask your healthcare provider or pharmacist for more information about VITRAKVI that is written for health professionals.

What are the ingredients in VITRAKVI?
Active ingredient: larotrectinib
Inactive ingredients:
Capsule: gelatin, titanium dioxide and edible ink
Oral Solution Packaged in One Bottle Containing 100 mL: purified water, hydroxypropyl betadex, sucrose, glycerin, sorbitol, citric acid, sodium phosphate, sodium citrate dihydrate, propylene glycol and flavoring. Preserved with methylparaben and potassium sorbate.
Oral Solution Packaged in Two Bottles Each Containing 50 mL: purified water, hydroxypropyl betadex, sucralose, sodium citrate, strawberry flavor, and citric acid. Preserved with sodium benzoate.
Manufactured for Bayer HealthCare Pharmaceuticals Inc., Whippany, NJ 07981
For more information, go to www.VITRAKVI.com or call 1-888-842-2937

This Patient Information has been approved by the U.S. Food and Drug Administration.

Revised: 4/2025

INSTRUCTIONS FOR USE
VITRAKVI (vi trak vee)
(larotrectinib)
oral solution

Read this Instructions for Use before you take or give a dose of VITRAKVI oral solution for the first time and each time you get a refill. There may be new information. This information does not take the place of talking with your healthcare provider about your medical condition or your treatment.

Your healthcare provider should show you how to correctly measure the prescribed dose of VITRAKVI oral solution before you take or give a dose for the first time.

Important information about measuring VITRAKVI oral solution:

- Always use the oral syringes provided with VITRAKVI to make sure that you correctly measure the prescribed dose.
- When you receive VITRAKVI oral solution from your healthcare provider or pharmacist, you will get a box that contains VITRAKVI oral solution. You may receive more than 1 box of VITRAKVI oral solution.
- Your healthcare provider or pharmacist will also provide you bottle adaptors and syringes. You will receive one bottle adaptor per bottle of VITRAKVI oral solution. After inserting the bottle adaptor into the bottle, do not remove the bottle adaptor.
- You will receive five 1 mL or 5 mL oral syringes that are marked to help you correctly measure the prescribed dose of VITRAKVI oral solution. Each oral syringe may be used over a 7-day period. Do not use a household teaspoon to measure the dose.

Supplies needed to take or give a dose of VITRAKVI oral solution

Figure A

How to prepare a dose of VITRAKVI oral solution:

Step 1: Remove the VITRAKVI oral solution bottle from the box. Place the bottle on a flat work surface. Open the bottle by pushing down firmly on the child-resistant cap and turning it in the direction of the arrow (counter-clockwise) See Figure B. Do not throw away the child-resistant cap.

Figure B

Step 2: Insert the bottle adaptor by pressing it into the bottle neck and make sure it is secure. See Figure C. Do not remove the bottle adaptor. If the bottle adaptor is missing, talk to your healthcare provider.

Figure C

Step 3: Remove the oral syringe from the wrapper. Throw the wrapper away in your household trash. Look at the markings on the barrel of the oral syringe and find the marking that matches the VITRAKVI oral solution dose in mL prescribed by your healthcare provider. See Figure D.

Figure D

Step 4: With the bottle on your flat work surface, use 1 hand to hold the bottle upright. Using your other hand, push the air out of the oral syringe by pushing the plunger down. Then, insert the tip of the oral syringe into the bottle adaptor at the top of the bottle. See Figure E. The tip of the oral syringe should fit snugly into the hole of the bottle adaptor.

Figure E

Step 5: Use 1 hand to hold the oral syringe in place. With the other hand, turn the bottle upside down. Pull back on the plunger until the top of the plunger lines up with the marking on the barrel of the oral syringe that matches the dose of VITRAKVI oral solution prescribed by your healthcare provider. See Figure F. Your dose may be different than the dose shown in Figure F.

Figure F

Step 6: Check for air bubbles in the oral syringe. If you see air bubbles, push up gently on the plunger to push any large air bubbles back into the bottle. Then, pull back on the plunger to the prescribed dose. See Figure G.

Figure G

Step 7: Turn the bottle upright again and place it on your work surface. Remove the oral syringe from the bottle adaptor by gently pulling up on the syringe barrel. See Figure H. Do not push on the plunger during this step. The bottle adaptor should stay attached to the bottle.

Figure H

Giving a dose of VITRAKVI oral solution by mouth:

Step 8: Place the tip of the oral syringe into the child's mouth against the inside of the cheek. Slowly squirt VITRAKVI oral solution into the mouth by pressing down on the plunger and allow the child to swallow. See Figure I.

- The child should be kept in an upright position for a few minutes right after giving a dose of VITRAKVI.
- If the child spits up a dose or you are not sure the entire dose was given, do not give another dose. Wait until the next scheduled dose.

Figure I

Step 9: Replace the child-resistant cap on the bottle of VITRAKVI oral solution. Do not remove the bottle adaptor. Close the bottle by turning the bottle cap in the direction of the arrow (clockwise). See Figure J.

Figure J

Cleaning instructions for oral syringes

Follow the instructions below for cleaning the oral syringe (Step 10 through Step 16). After 7 days of use, throw away the oral syringe in your household trash. Use a new oral syringe for the next 7 days.

Step 10: Remove plunger from the barrel of the oral syringe. See Figure K.

Figure K

Step 11: Rinse the barrel and plunger in warm running water to help make sure that all of the medicine has been removed from the oral syringe. See Figure L. Do not boil the oral syringe.

Figure L

Step 12: Re-insert the plunger into the barrel of the oral syringe. See Figure M.

Figure M

Step 13: Draw warm water several times into the oral syringe and squirt out again until all of the medicine has been removed from the oral syringe. See Figure N.

Figure N

Step 14: Repeat steps 10 and 11 to rinse the barrel and plunger again with warm water. See Figure O.

Figure O

Step 15: Shake off excess water or wipe off the outside. See Figure P. Place the barrel and plunger on a clean, dry paper towel to dry.

Figure P

Step 16: Repeat step 12 to assemble the oral syringe and store in a clean place until the next use.

Replace the oral syringe after 7 days of use, or if:

- there is any damage to the barrel, plunger, or tip
- the dosage marking is no longer clearly recognizable or
- it becomes difficult to move the plunger

How should I store VITRAKVI oral solution?

- Store VITRAKVI oral solution in a refrigerator between 36° F to 46° F (2° C to 8° C). Do not freeze.
- Write the date that you opened the bottle of VITRAKVI oral solution on the bottle. See Figure Q.
- Throw away (dispose of) any unused VITRAKVI oral solution:
  - Bottle of 100 mL: remaining 90 days after first opening the bottle
  - Bottle of 50 mL: remaining 31 days after first opening the bottle

Keep VITRAKVI oral solution and all medicines out of the reach of children.

Figure Q

Talk to your healthcare provider if you have questions about how to use VITRAKVI oral solution.

For more information, go to www.VITRAKVI.com or call 1-888-842-2937.

This Instructions for Use has been approved by the U.S. Food and Drug Administration.

Manufactured for Bayer HealthCare Pharmaceuticals Inc., Whippany, NJ 07981

Revised: 12/2022

Package Label - 25 mg - 60 Capsules

PRINCIPAL DISPLAY PANEL

NDC 71777-390-01

VITRAKVI®

(larotrectinib) capsules

25 mg

Usual Dosage: See prescribing information. Rx only.
60 capsules. Keep out of reach of children.
Store at 20°C to 25°C (68°F to 77°F).
Excursions permitted from 15°C to 30°C (59° to 86°F).

Manufactured for Loxo Omcology, Inc. Stamford, CT 06901 86579626

(01)10371777390012

Bayer

LOXO

Each capsule contains
25 mg larotrectinib
(equivalent to 30.7 mg
larotrectinib sulfate).

Package Label - 100 mg - 60 Capsules

PRINCIPAL DISPLAY PANEL

NDC 71777-391-01

VITRAKVI®

(larotrectinib) capsules

100 mg

Usual Dosage: See prescribing information.

Rx only. 60 capsules. Keep out of reach of children.
Store at 20°C to 25°C (68°F to 77°F).
Excursions permitted from 15°C to 30°C (59° to 86°F).

Manufactured for Loxo Omcology, Inc. Stamford, CT 06901 86579634

(01)10371777391019

Bayer

LOXO

Each capsule
contains 100 mg
larotrectinib
(equivalent to
123 mg
larotrectinib
sulfate).

PACKAGE LABEL

Package Label - 20 mg/mL - 100 mL Oral Solution

PRINCIPAL DISPLAY PANEL

NDC 71777-392-01

VITRAKVI®

(larotrectinib) oral solution

20 mg/mL

Usual Dosage: See prescribing information. Keep refrigerated. Store at 2°C to 8°C (36°F to 46°F). Rx only.
Date of first opening ____/____/____. Discard unused portion 90 days after first opening.
100 mL oral solution. Keep out of reach of children.

Manufactured for Loxo Omcology, Inc. Stamford, CT 06901 86659069

(01)10371777392016

Bayer

LOXO

Each bottle contains
100 ml of 20 mg/mL
larotrectinib (equivalent
to 24.6 mg/mL
larotrectinib sulfate).

Package/Label Display Panel

Package Label - 20 mg/mL - 50 mL Oral Solution

NDC 50419-393-02

VITRAKVI®

(larotrectinib) oral solution

20 mg/mL

RECOMMENDED DOSAGE: See prescribing information. Keep refrigerated. Store at 2°C to 8°C (36°F to 46°F). Rx only.
Date of first opening ____/____/____. Discard unused portion 31 days after first opening.
50 mL oral solution. For Oral Administration Only. Keep out of reach of children.

Manufactured for Bayer HealthCare Pharmaceuticals Inc., Whippany, NJ 07981 88735951

(01)10350419393024

Bayer

Each bottle contains
50 mL of 20 mg/mL
larotrectinib (equivalent
to 24.6 mg/mL
larotrectinib sulfate).